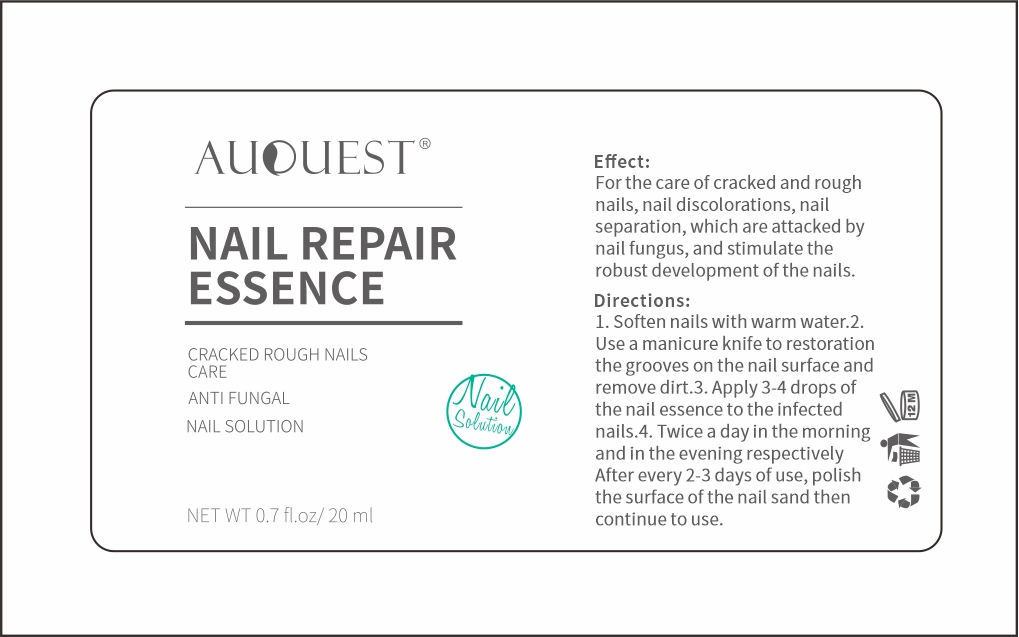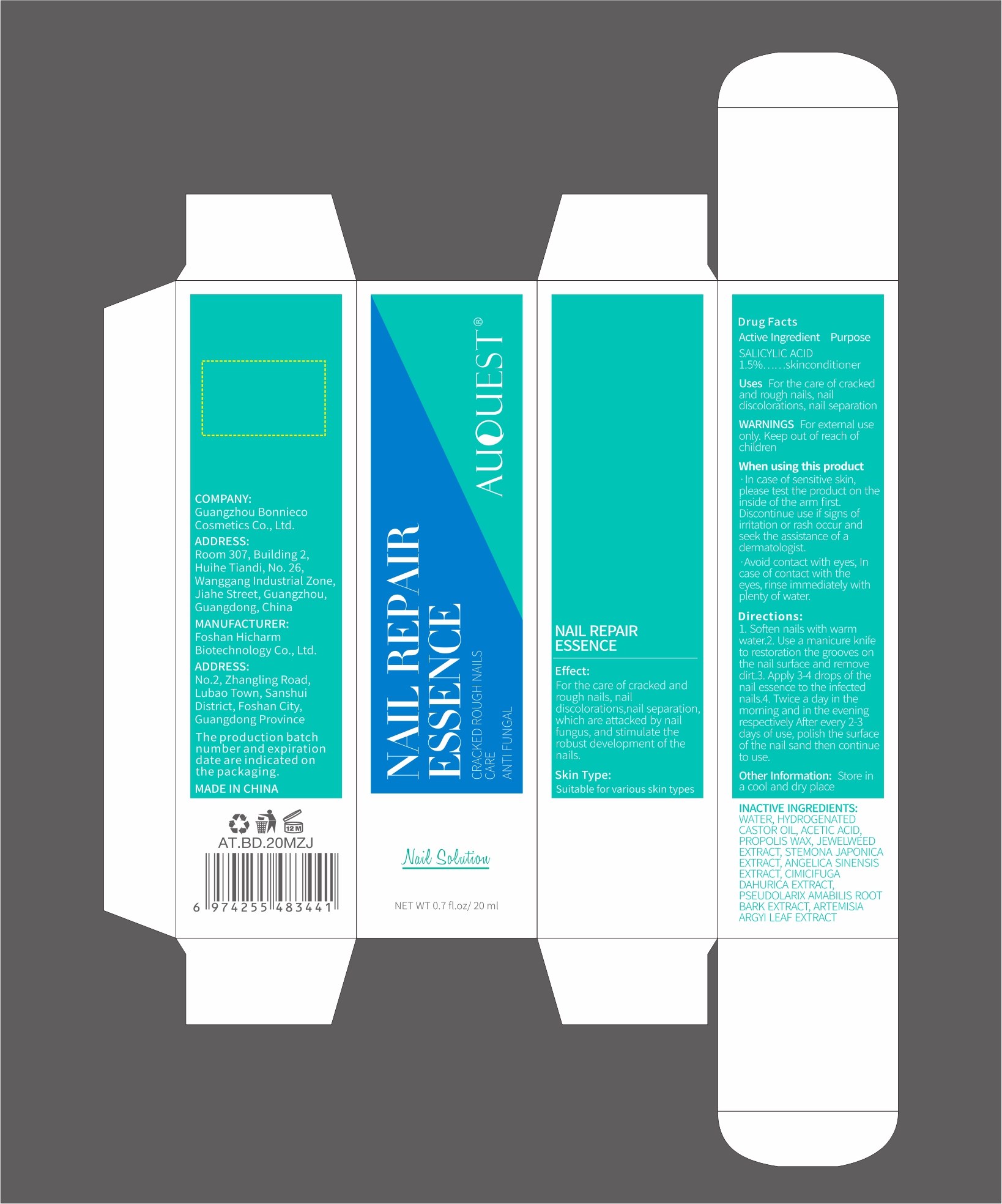 DRUG LABEL: AUQUEST NAIL REPAIRESSENCE
NDC: 84186-011 | Form: LIQUID
Manufacturer: Guangzhou Bonnieco Cosmetics Co., Ltd
Category: otc | Type: HUMAN OTC DRUG LABEL
Date: 20240402

ACTIVE INGREDIENTS: SALICYLIC ACID 5 g/100 mL
INACTIVE INGREDIENTS: WATER; ACETIC ACID; PROPOLIS WAX; IMPATIENS CAPENSIS LEAF; STEMONA JAPONICA ROOT; ANGELICA SINENSIS ROOT; HYDROGENATED CASTOR OIL; ARTEMISIA ARGYI LEAF; PSEUDOLARIX AMABILIS WHOLE; ACTAEA DAHURICA WHOLE

84186-011

Active Ingredient

Salicy Acid 1.5%

Purpose

skinconditioner, Antifungal

Use

For the care of crackedand rough nails, nail
discolorations, nail separation

Warnings

For external useonly. Keep out of reach ofchildren

Do not use

Discontinue use if signs ofirritation or rash occur andseek the assistance of adermatologist.

When Using

In case of contact with the eyes, rinse immediately with plenty of water.

Stop Use

If discomfort arises, please immediately stop using the product and seek the assistance of a dermatologist.

Ask Doctor

If discomfort arises, please immediately stop using the product and seek the assistance of a dermatologist.

Keep Oot Of Reach Of Children

Keep out of reach of children. If swallowed call emergency services.

Directions

1. Soften nails with warm water.2.Use a manicure knife to
2.repair the grooves on the nailsurface and remove dirt.
3.Apply 3-4 drops of the nailessence to the infected nails.4.Twice a day in the morningand in the evening respectively.After every 2-3 days of use,polish the surface of the nailsand then continue to use..

Other information

Store in a cool and dry place

Inactive ingredients

WATER, HYDROGENATED CASTOR OIL, ACETIC ACID, PROPOLIS WAX, JEWELWEED EXTRACT, STEMONA JAPONICA EXTRACT, ANGELICA SINENSIS EXTRACT, CIMICIFUGA DAHURICA EXTRACT, PSEUDOLARIX AMABILIS ROOT BARK EXTRACT, ARTEMISIA ARGYI LEAF EXTRACT